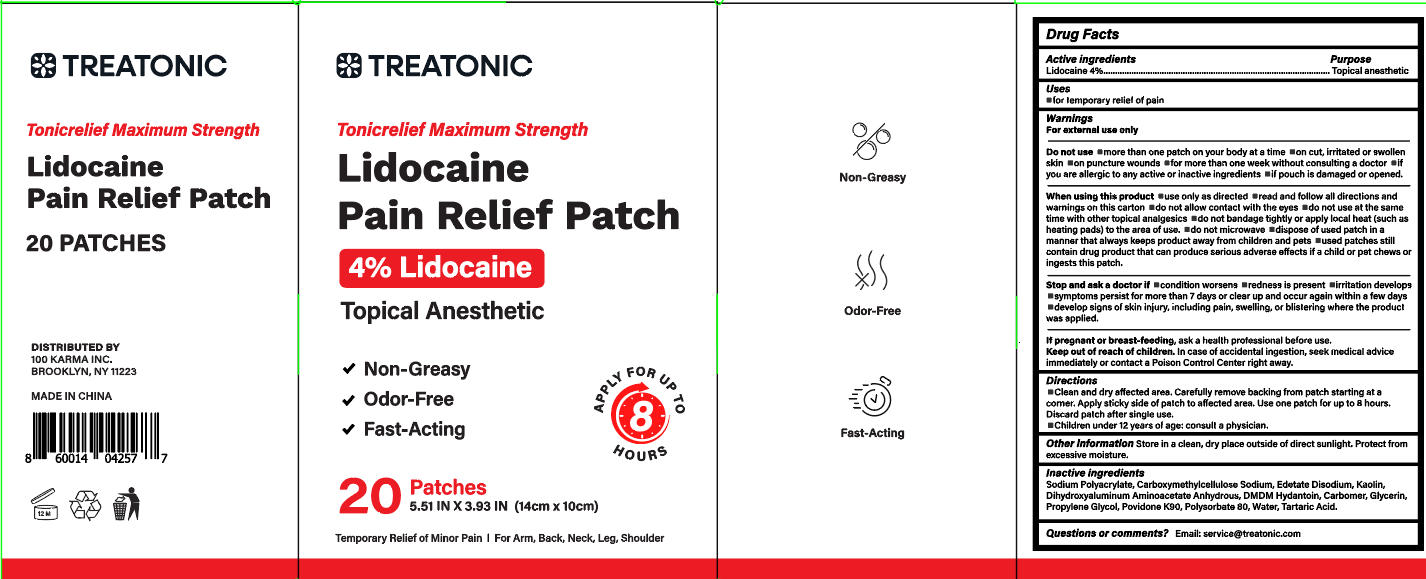 DRUG LABEL: Treatonic LIDOCAINE PAIN RELIEF
NDC: 85569-007 | Form: PATCH
Manufacturer: 100 KARMA INC
Category: otc | Type: HUMAN OTC DRUG LABEL
Date: 20250808

ACTIVE INGREDIENTS: LIDOCAINE 4 mg/100 1
INACTIVE INGREDIENTS: POLYSORBATE 80; WATER; CARBOXYMETHYLCELLULOSE SODIUM; POVIDONE K90; PROPYLENE GLYCOL; GLYCERIN; EDETATE DISODIUM; SODIUM POLYACRYLATE (2500000 MW); CARBOMER; TARTARIC ACID; KAOLIN; DMDM HYDANTOIN; DIHYDROXYALUMINUM AMINOACETATE ANHYDROUS

Initial Drug Listing - Treatonic LIDOCAINE PAIN RELIEF PATCH

ACTIVE INGREDIENT

Lidocaine 4%

PURPOSE

Topical anesthetic

DOSAGE AND ADMINISTRATION

for temporary relief of pain

WARNINGS

For external use only

DO NOT USE

- more than one patch on your body at a time
- on cut, irritated or swollenskin
- on puncture wounds
- for more than one week without consulting a doctor
- if you are allergic to any active or inactive ingredients
- if pouch is damaged or opened

WHEN USING

- use only as directed
- read and follow all directions and warnings on this carton
- do not allow contact with the eyes
- do not use at the same time with other topical analgesics
- do not bandage tightly or apply local heat (such asheating pads) to the area ofuse,
- do not microwave
- dispose of used patch in amanner that always keeps product away from children and pets
- used patches still contain drug product that can produce serious adverse effects if a child or pet chews or ingests this patch.

ASK DOCTOR

- condition worsens
- redness is present
- irritation develops
- symptoms persist for more than 7 days or clear up and occur again within a few days
- develop signs of skin injury, including pain, swelling, or blistering where the product was applied,

PREGNANCY OR BREAST FEEDING

ask a health professional before use

KEEP OUT OF REACH OF CHILDREN

In case of accidental ingestion, seek medical advice immediately or contact a Poison Control Center right away.

INDICATIONS AND USAGE

- Clean and dry affected area, Carefully remove backing from patch starting at a corner. Apply sticky side of patch to affected area. Use one patch for up to 8 hours. Discard patch after single use.
- Children under 12 years of age: consult a physician.

OTHER SAFETY INFORMATION

Store in a clean, dry place outside of direct sunlight. Protect from excessive moisture,

INACTIVE INGREDIENT

Sodium Polyacrylate, Carboxymethylcellulose Sodium, Edetate Disodium, Kaolin,Dihydroxyaluminum Aminoacetate Anhydrous, DMDM Hydantoin, Carbomer, Glycerin,Propylene Glycol, Povidone K90, Polysorbate 80, Water, Tartaric Acid.

QUESTIONS

Email: service@treatonic.com